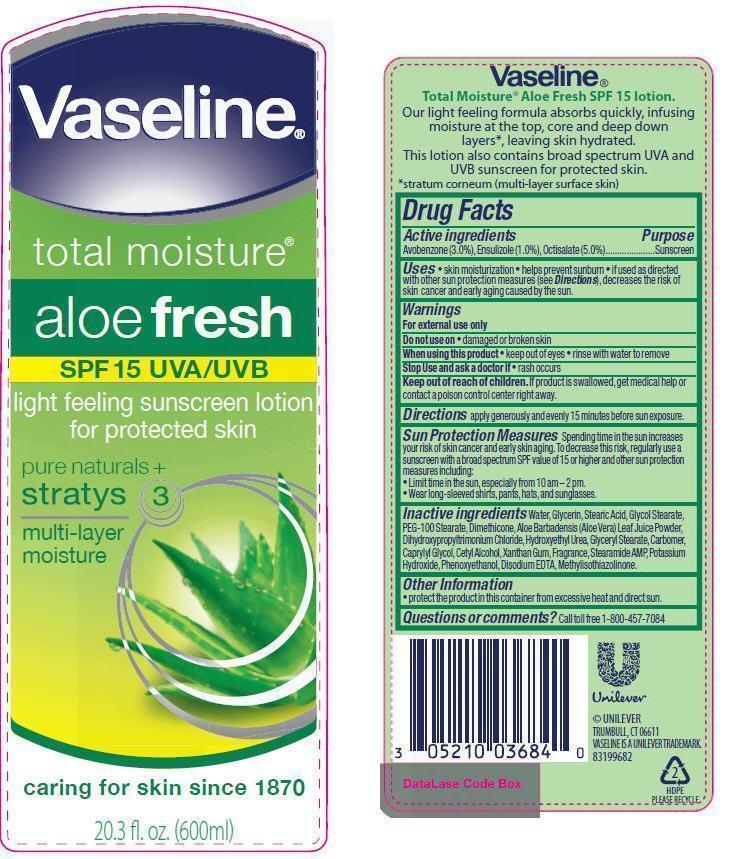 DRUG LABEL: Vaseline
NDC: 64942-1190 | Form: LOTION
Manufacturer: CONOPCO Inc. d/b/a Unilever
Category: otc | Type: HUMAN OTC DRUG LABEL
Date: 20121011

ACTIVE INGREDIENTS: OCTISALATE 50 mg/1 mL; AVOBENZONE 20 mg/1 mL; ENSULIZOLE 15 mg/1 mL; OCTOCRYLENE 13 mg/1 mL
INACTIVE INGREDIENTS: WATER; GLYCERIN; STEARIC ACID; GLYCOL STEARATE; PEG-100 STEARATE; DIMETHICONE; ALOE VERA LEAF; DIHYDROXYPROPYLTRIMONIUM CHLORIDE; .ALPHA.-TOCOPHEROL ACETATE, D-; GLYCERYL MONOSTEARATE; CAPRYLYL GLYCOL; CETYL ALCOHOL; XANTHAN GUM; STEARAMIDE AMP; POTASSIUM STEARATE; PHENOXYETHANOL; EDETATE DISODIUM; METHYLISOTHIAZOLINONE; BUTYLATED HYDROXYTOLUENE

Vaseline Total Moisture Aloe Fresh SPF 15

Active Ingredients
Avobenzone (2.0%), Ensulizole (1.5%), Octisalate (5.0%), Octocrylene (1.3%)

Purpose:
Sunscreen

Uses
∙ helps prevent sunburn
∙ if used as directed with other sun protection measures (see Directions), decreases the risk of skin cancer and early aging caused by the sun.

Warnings
For external use only

Do not use ∙ on damaged or broken skin

When using this product ∙ keep out of eyes ∙ rinse with water to remove

Stop Use and ask a doctor if · rash occurs

Keep out of reach of children. If swallowed, get medical help or contact a poison control center right away.

Directions

∙ apply generously and evenly 15 minutes before sun exposure.

∙ children under 6 months of age: Ask a doctor

∙ reapply at least every two hours

∙ use a water resistant sunscreen if swimming or sweating

Sun Protection Measures Spending time in the sun increases your risk of skin cancer and early skin aging. To decrease this risk, regularly use a sunscreen with a Broad Spectrum SPF value of 15 or higher and other sun protection measures including:

∙ Limit time in the sun, especially from 10 am - 2 pm

∙ Wear long-sleeved shirts, pants, hats, and sunglasses.

Inactive Ingredients
Water (Aqua), Glycerin, Stearic Acid, Glycol Stearate, PEG-100 Stearate, Dimethicone, Aloe Barbadensis (Aloe Vera) Leaf Juice Powder, Dihydroxypropyltrimonium Chloride,Tocopheryl Acetate, Phenoxyethanol, Glyceryl Stearate, Potassium Stearate, Carbomer, Cetyl Alcohol, Caprylyl Glycol, Xanthan Gum,Fragrance (Parfum), Disodium EDTA, BHT, Stearamide AMP, Methylisothiazolinone.

QUESTIONS

1-800-457-7084

PACKAGE LABEL

PDP 20.3 fl. oz.